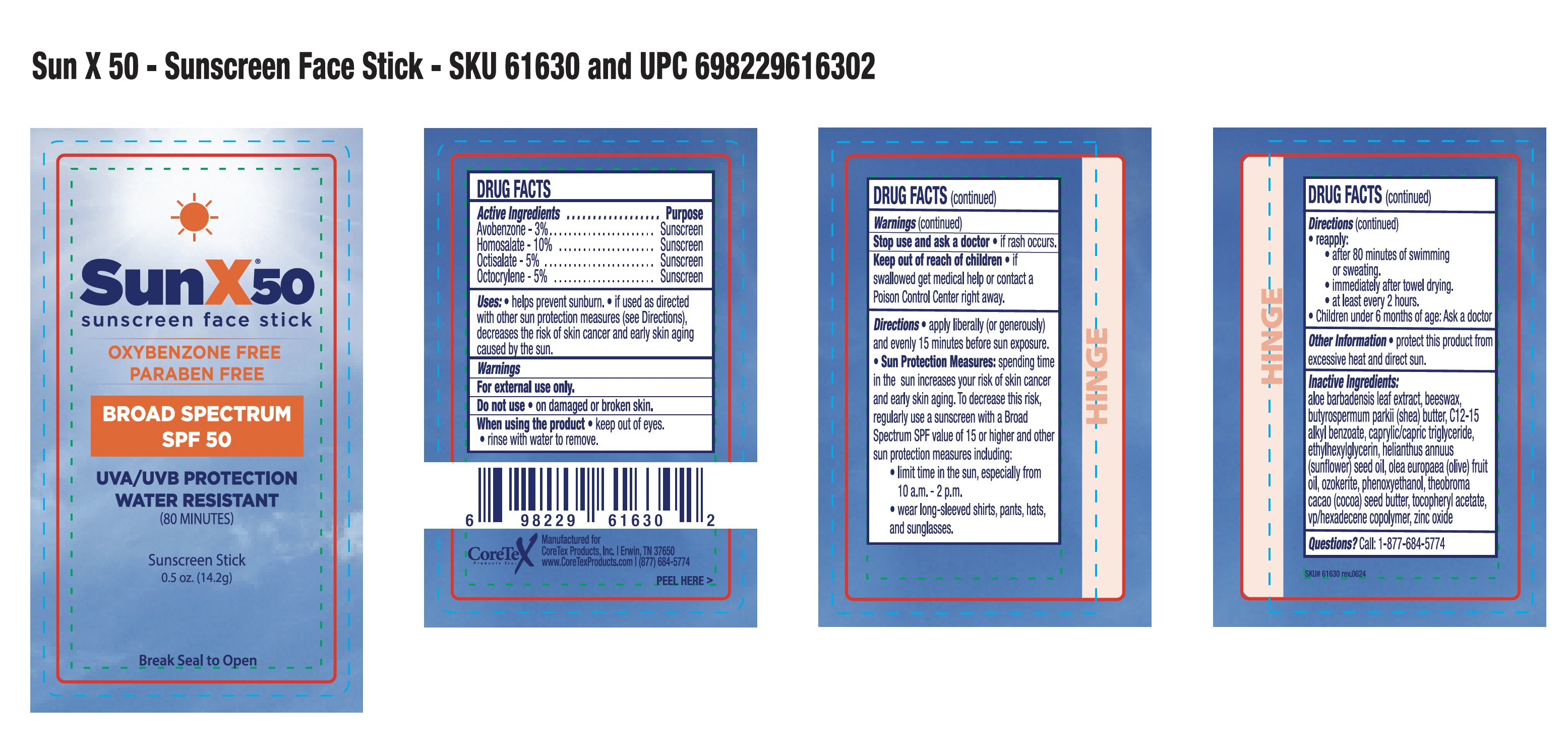 DRUG LABEL: CoreTex Sun X 50 Sunscreen Face Stick
NDC: 65753-604 | Form: STICK
Manufacturer: CoreTex Products Inc
Category: otc | Type: HUMAN OTC DRUG LABEL
Date: 20241005

ACTIVE INGREDIENTS: OCTISALATE 5 g/100 g; AVOBENZONE 3 g/100 g; HOMOSALATE 10 g/100 g; OCTOCRYLENE 5 g/100 g
INACTIVE INGREDIENTS: VINYLPYRROLIDONE/HEXADECENE COPOLYMER; ZINC OXIDE; PARAFFIN; SHEA BUTTER; SUNFLOWER SEED OIL GLYCERETH-8 ESTERS; OLIVE OIL; CAPRYLIC/CAPRIC/LAURIC TRIGLYCERIDE; WHITE WAX; THEOBROMA CACAO WHOLE; .ALPHA.-TOCOPHEROL ACETATE; ALKYL (C12-15) BENZOATE; ALOE VERA LEAF; ETHYLHEXYLGLYCERIN; PHENOXYETHANOL

Sun X 50 Sunscreen Face Stick
65753-604

Active ingredients

Avobenzone...3%

Homosalate...10%

Octisalate...5%

Octocrylene...5%

Purpose

Sunscreen

Sunscreen

Sunscreen

Sunscreen

Uses:

- helps prevent sunburn.
- if used as directed with other sun protection measures (see Directions), decreases the risk of skin cancer and early skin aging caused by the sun.

Warnings

For external use only.

Do not use

- on damaged or broken skin

When using this product

- keep out of eyes.
- rinse with water to remove.

Stop use and ask a doctor

- if rash occurs.

Keep out of reach of children

- if swallowed get medical help or contact a Poison Control Center right away.

Directions

apply liberally (or generously) and evenly 15 minutes before sun exposure.

- Sun Protection Measures: spending time in the sun increases your risk of skin cancer and early skin aging. To decrease this risk, regularly use sunscreen with a Broad Spectrum SPF value of 15 or higher and other sun protection measures including:
- limit time in the sun, especially from 10 a.m. -2 p.m.
- wear long-sleaved shirts, pants, hats and sunglasses.
- reapply:
- after 80 minutes of swimming or sweating.
- immediately after towel drying.
- at least every 2 hours.
- Children under 6 months of age: Ask a doctor

Other information

- protect this product from excessive heat and direct sun.

Inactive ingredients

aloe barbadensis leaf extract, beeswax, butyrospermum parkii (shea) butter, CI2-15 alkyl benzoate, capryilc/capric triglyceride, ethylhexylglycerin, helianthus annuus (sunflower) seed oil, olea europaea (olive) fruit oil, ozokerite, phenoxyethanol, theobroma cacao (cocoa) seed butter, tocopheryl acetate, vp/hexadecene copolymer, zinc oxide

Questions?

Call: 1-877-684-5774